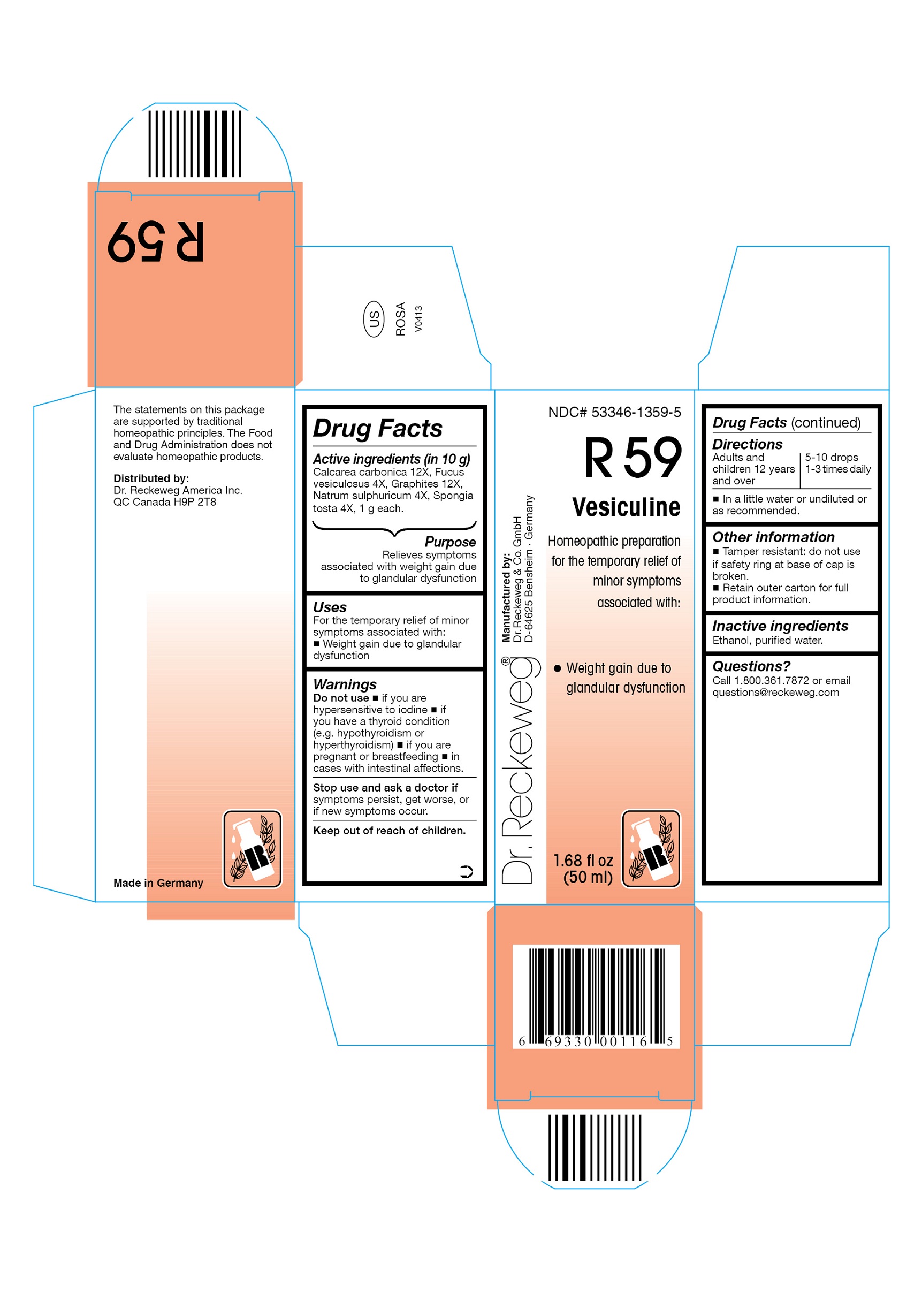 DRUG LABEL: DR. RECKEWEG R59 Vesiculine
NDC: 53346-1359 | Form: LIQUID
Manufacturer: PHARMAZEUTISCHE FABRIK DR. RECKEWEG & CO
Category: homeopathic | Type: HUMAN OTC DRUG LABEL
Date: 20130404

ACTIVE INGREDIENTS: OYSTER SHELL CALCIUM CARBONATE, CRUDE 12 [hp_X]/50 mL; FUCUS VESICULOSUS 4 [hp_X]/50 mL; GRAPHITE 12 [hp_X]/50 mL; SODIUM SULFATE 4 [hp_X]/50 mL; SPONGIA OFFICINALIS SKELETON, ROASTED 4 [hp_X]/50 mL
INACTIVE INGREDIENTS: ALCOHOL; WATER

DR. RECKEWEG R59 Vesiculine

Active ingredients

Calcarea carbonica 12X, Fucus vesiculosus 4X, Graphites 12X, Natrum sulphuricum 4X, Spongia tosta 4X, 1 g each in 10 g.

Purpose

Relieves symptoms associated with weight gain due to glandular dysfunction

Uses

For the temporary relief of minor symptoms associated with:

- Weight gain due to glandular dysfunction

Warnings

Do not use

- if you are hypersensitive to iodine
- if you have a thyroid condition (e.g. hypothyroidism or hyperthyroidism)
- if you are pregnant or breastfeeding
- in cases with intestinal affections

Stop use and ask a doctor if symptoms persist, get worse, or if new symptoms occur.

Keep out of reach of children.

Directions

Adults and children ≥ 12 years 5-10 drops 1-3 times daily in a little water or undiluted or as recommended.

Other information

- Tamper resistant: do not use if safety ring at base of cap is broken.
- Retain outer carton for full product instructions.

Inactive ingredients

Ethanol, purified water.

Questions?
Call 1-800-361-7872 or email questions@reckeweg.com

PACKAGE LABEL

NDC# 53346-1359-5

Dr. Reckeweg R59 Vesiculine

Homeopathic preparation for the temporary relief of minor symptoms associated with:

- Weight gain due to glandular dysfunction

Manufactured by:

Dr. Reckeweg Co. GmbH

D-64625 Bensheim

Germany

1.68 fl oz
(50 ml)